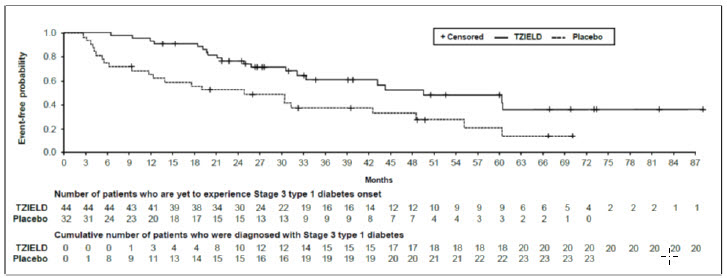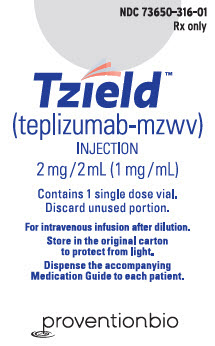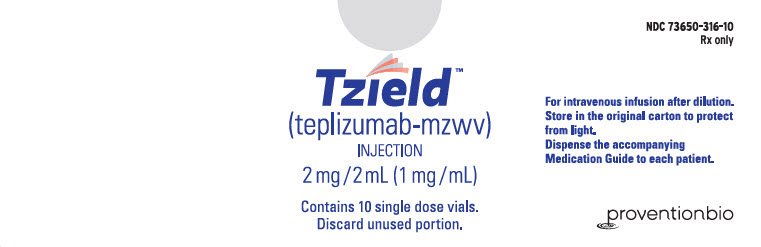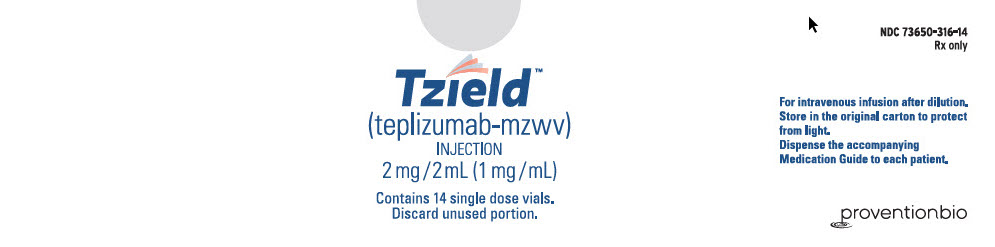 DRUG LABEL: TZIELD
NDC: 73650-316 | Form: INJECTION
Manufacturer: Provention Bio, Inc.
Category: prescription | Type: HUMAN PRESCRIPTION DRUG LABEL
Date: 20250506

ACTIVE INGREDIENTS: TEPLIZUMAB 1 mg/1 mL
INACTIVE INGREDIENTS: SODIUM PHOSPHATE, DIBASIC, DODECAHYDRATE 0.26 mg/1 mL; SODIUM PHOSPHATE, MONOBASIC, DIHYDRATE 1.13 mg/1 mL; SODIUM CHLORIDE 8.78 mg/1 mL; POLYSORBATE 80 0.05 mg/1 mL; WATER

HIGHLIGHTS OF PRESCRIBING INFORMATION

These highlights do not include all the information needed to use TZIELD safely and effectively. See full prescribing information for TZIELD.
TZIELD® (teplizumab-mzwv) injection, for intravenous use
Initial U.S. Approval: 2022

1 INDICATIONS AND USAGE

TZIELD is a CD3-directed antibody indicated to delay the onset of Stage 3 type 1 diabetes (T1D) in adults and pediatric patients aged 8 years and older with Stage 2 T1D (1).

2 DOSAGE AND ADMINISTRATION

- Confirm Stage 2 T1D by documenting at least two positive pancreatic islet autoantibodies in those who have dysglycemia without overt hyperglycemia using an oral glucose tolerance test (OGTT) or alternative method if appropriate and OGTT is not available (2.1).
- In patients who meet criteria for a diagnosis of Stage 2 type 1 diabetes, ensure the clinical history of the patient does not suggest type 2 diabetes (2.1).
- Prior to initiating TZIELD, obtain a complete blood count and liver enzyme tests. Use of TZIELD is not recommended in patients with certain laboratory abnormalities (2.2).
- Must dilute TZIELD in 0.9% Sodium Chloride Injection, USP. See full prescribing information for detailed preparation and administration instructions (2.3, 2.4, 2.5).
- Premedicate with: (1) a nonsteroidal anti-inflammatory drug (NSAID) or acetaminophen, (2) an antihistamine, and/or (3) an antiemetic before each TZIELD dose for at least the first 5 days of the 14-day treatment course (2.3).
- Administer TZIELD by intravenous infusion (over a minimum of 30 minutes) once daily for 14 days. See full prescribing information for the dosing schedule (2.4).

3 DOSAGE FORMS AND STRENGTHS

- Injection: 2 mg per 2 mL (1 mg/mL) single-dose vial (3).

4 CONTRAINDICATIONS

- None. (4).

5 WARNINGS AND PRECAUTIONS

- Cytokine Release Syndrome (CRS): Premedicate, monitor liver enzymes, discontinue in those that develop elevated ALT or AST more than 5 times the upper limit of normal, and if severe CRS develops consider temporarily pausing dosing (5.1).
- Serious Infections: Use of TZIELD is not recommended in patients with active serious infection or chronic infection. Monitor for signs and symptoms of infection during and after TZIELD treatment. If a serious infection develops, discontinue TZIELD (5.2).
- Lymphopenia: Monitor white blood cell counts during the treatment period. If prolonged severe lymphopenia (<500 cells per mcL lasting 1 week or longer) develops, discontinue TZIELD (5.3).
- Hypersensitivity Reactions: If severe hypersensitivity reactions occur, discontinue TZIELD and treat promptly (5.4).
- Vaccinations: Administer all age-appropriate vaccinations prior to starting TZIELD. See recommendations regarding live-attenuated, inactivated, and mRNA vaccines (2.2, 5.5).

6 ADVERSE REACTIONS

Most common adverse reactions (>10%) were lymphopenia, rash, leukopenia and headache (6.1).

To report SUSPECTED ADVERSE REACTIONS, contact Provention Bio at 1-800-633-1610 or FDA at 1-800-FDA-1088 or www.fda.gov/medwatch

8 USE IN SPECIFIC POPULATIONS

- Pregnancy: May cause fetal harm (8.1).
- Lactation: A lactating woman may consider pumping and discarding breast milk during and for 20 days after TZIELD administration (8.2).

FULL PRESCRIBING INFORMATION

1 INDICATIONS AND USAGE

TZIELD is indicated to delay the onset of Stage 3 type 1 diabetes in adults and pediatric patients 8 years of age and older with Stage 2 type 1 diabetes [see Dosage and Administration (2.1)].

2 DOSAGE AND ADMINISTRATION

2.1 Patient Selection

Select adult patients and pediatric patients 8 years of age and older for TZIELD treatment who have a diagnosis of Stage 2 type 1 diabetes.

- Confirm Stage 2 type 1 diabetes by documenting:
  - At least two positive pancreatic islet cell autoantibodies
  - Dysglycemia without overt hyperglycemia using an oral glucose tolerance test (if an oral glucose tolerance test is not available, an alternative method for diagnosing dysglycemia without overt hyperglycemia may be appropriate)
- Ensure the clinical history of the patient does not suggest type 2 diabetes.

2.2 Laboratory Evaluation and Vaccination Prior to Initiation

- Prior to initiating TZIELD, obtain a complete blood count and liver enzyme tests.
- Use of TZIELD is not recommended in patients with [see Warnings and Precautions (5)]:
  - Lymphocyte count less than 1,000 lymphocytes/mcL
  - Hemoglobin less than 10 g/dL
  - Platelet count less than 150,000 platelets/mcL
  - Absolute neutrophil count less than 1,500 neutrophils/mcL
  - Elevated ALT or AST greater than 2 times the upper limit of normal (ULN) or bilirubin greater than 1.5 times ULN
  - Laboratory or clinical evidence of acute infection with Epstein-Barr virus (EBV) or cytomegalovirus (CMV)
  - Active serious infection or chronic active infection other than localized skin infections
- Administer all age-appropriate vaccinations prior to starting TZIELD [see Warnings and Precautions (5.5)]:
  - Administer live-attenuated (live) vaccines at least 8 weeks prior to treatment.
  - Administer inactivated (killed) vaccines or mRNA vaccines at least 2 weeks prior to treatment.

2.3 Important Preparation and Premedication Instructions

The following are important preparation and premedication instructions:

- Must dilute TZIELD prior to use [see Dosage and Administration (2.5)].
- Premedicate prior to TZIELD infusion for the first 5 days of dosing with: (1) a nonsteroidal anti-inflammatory drug (NSAID) or acetaminophen, (2) an antihistamine, and/or (3) an antiemetic [see Warnings and Precautions (5.1)]. Administer additional doses of premedication if needed.

2.4 Recommended Dosage and Administration

Administer TZIELD by intravenous infusion (over a minimum of 30 minutes), using a body surface area-based dosing, once daily for 14 consecutive days as follows:

- Day 1: 65 mcg/m^2
- Day 2: 125 mcg/m^2
- Day 3: 250 mcg/m^2
- Day 4: 500 mcg/m^2
- Days 5 through 14: 1,030 mcg/m^2

Do not administer two doses on the same day.

Recommendations Regarding Missed Dose(s)
If a planned TZIELD infusion is missed, resume dosing by administering all remaining doses on consecutive days to complete the 14-day treatment course.

2.5 Additional Preparation and Administration Instructions

The following are additional preparation and administration instructions [see Dosage and Administration (2.2, 2.3, 2.4)]:

- Inspect TZIELD visually before use (the supplied solution is clear and colorless). Do not use TZIELD if particulate matter or coloration is seen.
- Prepare TZIELD using aseptic technique. Each vial is intended for single dose only.
- Prepare a:
  - Sterile glass vial with 18 mL of 0.9% Sodium Chloride Injection or
  - Polyvinylchloride (PVC) infusion bag with 18 mL of 0.9% Sodium Chloride Injection.
- Remove 2 mL of TZIELD from the vial and slowly add to the 18 mL of 0.9% Sodium Chloride Injection. Mix gently by slowly inverting the vial or rocking the infusion bag. The resulting 20 mL diluted solution contains 100 mcg/mL of teplizumab-mzwv.
- Using an appropriately sized syringe (e.g., 5 mL), withdraw the volume of diluted TZIELD solution required for that day's calculated dose from the 100 mcg/mL solution.
- Slowly add contents of the syringe containing the TZIELD dose to a 25 mL 0.9% Sodium Chloride Injection PVC infusion bag. Gently rock the infusion bag to ensure that the solution mixes sufficiently. Do not shake.
- Discard unused portion of remaining diluted TZIELD solution in the sterile glass vial or PVC infusion bag.
- Start the TZIELD infusion within 2 hours of preparation. If not used immediately, store the infusion solution at room temperature [15°C to 30°C (59°F to 86°F)] and complete infusion within 4 hours of the start of preparation. Discard the infusion solution if not administered within 4 hours of preparation.

3 DOSAGE FORMS AND STRENGTHS

Injection: 2 mg per 2 mL (1 mg/mL) clear and colorless solution in a single-dose vial.

4 CONTRAINDICATIONS

None.

5 WARNINGS AND PRECAUTIONS

5.1 Cytokine Release Syndrome

Cytokine release syndrome (CRS) has been observed in TZIELD-treated patients. In clinical trials, CRS was reported in 5% of TZIELD-treated patients compared to 0.8% of control-treated patients during the treatment period and through 28 days after the last study drug administration. CRS manifestations in TZIELD-treated patients included fever, nausea, fatigue, headache, myalgia, arthralgia, increased alanine aminotransferase (ALT), increased aspartate aminotransferase (AST), and increased total bilirubin. These manifestations typically occurred during the first 5 days of TZIELD treatment [see Adverse Reactions (6.1)]. To mitigate CRS:

- Premedicate with antipyretics, antihistamines and/or antiemetics prior to TZIELD treatment [see Dosage and Administration (2.3)].
- Monitor liver enzymes during treatment. Discontinue TZIELD treatment in patients who develop elevated ALT or AST more than 5 times the upper limit of normal (ULN) or bilirubin more than 3 times ULN.
- Treat symptoms of CRS with antipyretics, antihistamines and/or antiemetics. If severe CRS develops, consider temporarily pausing dosing for 1-2 days (and administer the remaining doses to complete the full 14-day course on consecutive days) or discontinuing treatment.

5.2 Serious Infections

Bacterial and viral infections have occurred in TZIELD-treated patients. In clinical trials, TZIELD-treated patients had a higher rate of serious infections (3.5%) than control-treated patients (2%), including gastroenteritis, cellulitis, pneumonia, abscess, sepsis [see Adverse Reactions (6.1)]. Use of TZIELD is not recommended in patients with active serious infection or chronic infection other than localized skin infections. Monitor patients for signs and symptoms of infection during and after TZIELD treatment. If serious infection develops, treat appropriately, and discontinue TZIELD.

5.3 Lymphopenia

In clinical trials, 78% of TZIELD-treated patients developed lymphopenia compared to 11% of control-treated patients. For most TZIELD-treated patients who experienced lymphopenia, lymphocyte levels began to recover after the fifth day of treatment and returned to pre-treatment values within two weeks after treatment completion and without dose interruption. Severe lymphopenia (<500 cells per mcL) lasting 1 week or longer occurred in 0.9% of TZIELD-treated patients, and 0.5% of TZIELD-treated patients permanently discontinued TZIELD because of lymphopenia [see Adverse Reactions (6.1)].

Monitor white blood cell counts during the treatment period. If prolonged severe lymphopenia (<500 cells per mcL lasting 1 week or longer) develops, discontinue TZIELD.

5.4 Hypersensitivity Reactions

Acute hypersensitivity reactions including serum sickness, angioedema, urticaria, rash, vomiting and bronchospasm occurred in TZIELD-treated patients [see Adverse Reactions (6.1)]. If severe hypersensitivity reactions occur, discontinue use of TZIELD and treat promptly.

5.5 Vaccinations

The safety of immunization with live-attenuated vaccines in TZIELD-treated patients has not been studied. Additionally, TZIELD may interfere with the immune response to vaccination and decrease vaccine efficacy.

- Administer all age-appropriate vaccinations prior to starting TZIELD [see Dosage and Administration (2.2)].
- Inactivated or mRNA vaccinations are not recommended within the 2 weeks prior to TZIELD treatment, during treatment, or 6 weeks after completion of treatment.
- Live-attenuated vaccinations are not recommended within the 8 weeks prior to TZIELD treatment, during treatment, or up to 52 weeks after treatment.

6 ADVERSE REACTIONS

The following serious adverse reactions are described elsewhere in the Prescribing Information:

- Cytokine Release Syndrome [see Warnings and Precautions (5.1)]
- Serious Infections [see Warnings and Precautions (5.2)]
- Lymphopenia [see Warnings and Precautions (5.3)]
- Hypersensitivity Reactions [see Warnings and Precautions (5.4)]

6.1 Clinical Trials Experience

Because clinical trials are conducted under widely varying conditions, adverse reaction rates observed in the clinical trials of a drug cannot be directly compared to rates in the clinical trials of another drug and may not reflect the rates observed in practice.

Placebo-Controlled Study in Patients with Stage 2 Type 1 Diabetes
The data in Table 1 are derived from the placebo-controlled study (Study TN-10) in patients aged 8 years and older with Stage 2 type 1 diabetes (T1D) [see Clinical Studies (14)]. These data reflect exposure of 44 patients of whom 93% completed the full 14-day treatment course.

Pool of Five Controlled Clinical Studies in Stage 2 Type 1 Diabetes and in an Unapproved Population
Adverse reactions in TZIELD-treated patients were also evaluated in a larger pool of adult and pediatric patients who participated in five controlled clinical studies (including Study TN-10 described above):

- One study in patients with Stage 2 T1D (Study TN-10) [see Clinical Studies (14)],
- Three placebo-controlled studies in an unapproved population,
- One open-label standard-of-care controlled study of TZIELD in an unapproved population.

In this pool:

- 773 patients received TZIELD (44 patients with Stage 2 TID and 729 patients from an unapproved population), and
- 245 patients received either placebo or standard of care control (32 patients with Stage 2 T1D and 213 patients from an unapproved population).

In these studies, 436 patients received a 14-day dosing regimen of TZIELD with a total drug exposure that was comparable to the total drug exposure achieved with the recommended dosage [see Dosage and Administration (2.4)], 168 patients received a 14-day course of TZIELD with a lower total TZIELD drug exposure, and 169 patients received a 6-day course of TZIELD with a lower total TZIELD drug exposure. The mean age of TZIELD-treated patients was 17.6 years (median 15 years), 62% were <18 years old (40% age 12 to 17; 21% age 8 to 11), and 64% were male. The population was 72% White, 26% Asian, 1% Black or African American, 1% were multiple or unknown race, and <1% American Indian or Alaska Native; 5% were Hispanic or Latino ethnicity.

Common Adverse Reactions
Table 1 presents common (≥ 5%) adverse reactions that occurred during treatment and through 28 days after the last study drug administration in Study TN-10. Adverse reactions observed in pediatric patients 8 years and older who received TZIELD were consistent with those reported in adult patients in this study.

Table 1. Common Adverse Reactions [That occurred during treatment and through 28 days after the last study drug administration] in Adult and Pediatric Patients Aged 8 Years and Older with Stage 2 Type 1 Diabetes (Study TN-10) [Adverse reactions that occurred in 2 or more TZIELD-treated patients]
Adverse Reaction | Placebo N=32 | TZIELD N=44
Lymphopenia | 6% | 73%
Rash [Composite of rash-related terms including rash erythematous, rash macular, rash papular, rash maculo-papular, rash pruritic] | 0% | 36%
Leukopenia | 0% | 21%
Headache | 6% | 11%
Neutropenia | 3% | 5%
Increased alanine aminotransferase | 3% | 5%
Nausea | 3% | 5%
Diarrhea | 0% | 5%
Nasopharyngitis | 0% | 5%

Cytokine Release Syndrome (CRS)
In Study TN-10, CRS was reported in 2% of TZIELD-treated patients compared to 0% of placebo-treated patients.

Of the 39 TZIELD-treated patients that developed CRS (5% of all TZIELD-treated patients) in the pool of 5 clinical trials, 13% of the CRS cases were serious adverse reactions [see Warnings and Precautions (5.1)]. Liver transaminase elevations were observed in 56% of TZIELD-treated patients who experienced CRS: 64% were up to 2.5 times ULN, 32% were more than 2.5 to 5 times ULN, and 4.5% were 5-10 times ULN.

Serious Infections
In Study TN-10, serious infections (cellulitis, gastroenteritis, pneumonia, wound infection) were reported in 9% (4/44) of TZIELD-treated patients compared to 0% (0/32) of placebo-treated patients any time during or after the first dose of study treatment.

Rash and Hypersensitivity Reactions
Hypersensitivity reactions were reported with TZIELD in Study TN-10. Serum sickness was observed in 2% (1/44) of TZIELD-treated patients compared to 0% (0/32) of placebo-treated patients. The patient who developed serum sickness had a prior history of positive anti-nuclear antibody and presented with arthralgias and elevated c-reactive protein and low C4 complement five days after completing their course of TZIELD; illness resolved in 2.5 months.

In the pool of 5 clinical trials of patients:

- Anaphylaxis (with hypoxia and bronchospasm) was observed in one TZIELD-treated patient who was hospitalized.
- Angioedema (periorbital and facial) was observed in 0.3% TZIELD-treated patients, compared to 0% in control-treated patients. Peripheral and generalized edema was reported in 1.6% of TZIELD-treated patients and 0% of control-treated patients.
- Rash was observed in 48% of TZIELD-treated patients compared to 15% in control-treated patients, with 33 excess cases of rash per 100 patients. The majority of rashes observed with TZIELD treatment were not serious and resolved without intervention; although 0.3% (2/773) of TZIELD-treated patients had a serious rash compared to 0% (0/245) of placebo- treated patients.
- Urticaria was reported in 1.9% of TZIELD-treated patients and in 1.2% of control-treated patients.

Immunogenicity: Anti-Drug Antibody-Associated Adverse Reactions
In Study TN-10, rash occurred in 39% of TZIELD-treated patients who developed anti- teplizumab-mzwv antibodies and in 33% of TZIELD-treated patients who did not develop anti- teplizumab-mzwv antibodies [see Clinical Pharmacology (12.6)].

Other Adverse Reactions
Lymphopenia
In Study TN-10, lymphopenia was reported in 73% of TZIELD-treated patients compared to 6% of placebo-treated patients. The average lymphocyte count nadir occurred at Day 5 of treatment, with recovery and return to baseline by Week 6 [see Warnings and Precautions (5.3)].

Neutropenia
In Study TN-10, neutropenia was observed in 7% of TZIELD-treated patients compared to 3% of placebo-treated patients.

Anemia and Thrombocytopenia
In the pool of 5 clinical trials of patients, anemia was reported in 27% of TZIELD-treated patients compared to 21% of placebo-treated patients, and thrombocytopenia was reported in 13% of TZIELD-treated patients compared to 5% of placebo-treated patients during the 14-day treatment course; recovery occurred within 2 to 4 weeks of treatment. In clinical trials, 1.8% of TZIELD-treated patients discontinued treatment due to hemoglobin less than 8.5 g/dL (or a decrease of more than 2 g/dL to a value less than 10 g/dL), and 1% discontinued TZIELD due to platelet count less than 50,000 platelets/mcL.

Liver Enzyme Elevations
Liver enzyme elevations were observed in TZIELD-treated patients, both in the context of CRS and in patients without CRS. In the pool of 5 clinical trials, elevated aminotransferases were reported in 25% of TZIELD-treated patients compared to 11% of placebo-treated patients during the 14-day treatment course. On laboratory analysis, 5.1% of TZIELD-treated patients experienced a peak ALT more than 3 times the ULN compared to 0.8% of control-treated patients. Most liver enzyme elevations were transient and resolved 1-2 weeks after treatment; 98% resolved by follow-up week 14.

Other Laboratory Abnormalities
In the pool of 5 clinical trials, other laboratory abnormalities including decreased bicarbonate (15% in TZIELD-treated patients, compared to 7% in placebo-treated patients) and decreased blood calcium (19% in TZIELD-treated patients, compared to 13% in placebo-treated patients) were noted.

8 USE IN SPECIFIC POPULATIONS

8.1 Pregnancy

Risk Summary
Available case reports from clinical trials with TZIELD are insufficient to identify a drug- associated risk of major birth defects, miscarriage or other adverse maternal or fetal outcomes. Although there are no data on teplizumab-mzwv, monoclonal antibodies can be actively transported across the placenta, and TZIELD may cause immunosuppression in the utero- exposed infant (see Clinical Considerations). To minimize exposure to a fetus, avoid use of TZIELD during pregnancy and at least 30 days (6 half-lives) prior to planned pregnancy.

TZIELD is not active in rodents. In animal reproduction studies, mice were given a surrogate anti-mouse CD3 antibody subcutaneously during organogenesis through lactation. Pups born to dams administered the murine surrogate antibody during pregnancy showed a reduction in the adaptive immune response consistent with the expected pharmacology (see Data).

The estimated background risk of major birth defects and miscarriage for the indicated population is unknown. In the U.S. general population, the background risk of major birth defects and miscarriage in clinically recognized pregnancies is 2%-4% and 15%-20%, respectively.

Report pregnancies to Provention Bio, Inc.'s Adverse Event reporting line at 1-800-633-1610.

Clinical Considerations
Fetal/Neonatal Adverse Reactions
Transport of endogenous IgG antibodies across the placenta increases as pregnancy progresses, and peaks during the third trimester. Because teplizumab-mzwv may interfere with immune response to infections, risks and benefits should be considered prior to administering live vaccines to infants exposed to teplizumab-mzwv in utero. There are insufficient data regarding infant serum levels of teplizumab-mzwv at birth and the duration of persistence of teplizumab- mzwv in infant serum after birth to identify a specific timeframe to delay live virus immunizations in infants exposed in utero.

Data
Animal Data
In an embryo-fetal developmental toxicity study, pregnant mice were administered a murine surrogate anti-mouse CD3 antibody by subcutaneous injection at dose levels of 0, 0.03, 0.3, or 20 mg/kg on Gestation Days 6, 10, and 14. Increase in post-implantation loss occurred in the 20 mg/kg group, in the presence of maternal toxicity.

In a pre- and postnatal development toxicity study in pregnant mice, in which the murine surrogate antibody was administered every 3 days from gestation day 6 through lactation day 19 at doses of 0, 0.3, 3, or 20 mg/kg, no maternal toxicity or increased incidence of post- implantation loss was observed. Reductions in T cell populations and increases in B cells, and a reduction in the adaptive immune response to keyhole limpet hemocyanin (KLH) were observed in the offspring on postnatal days 35 and 84 at 20 mg/kg. The surrogate antibody was present in the offspring serum at level less than 1.5% that of maternal serum at the high dose. A trend towards reduction in fertility was observed in the offspring of dams administered the murine surrogate antibody at 20 mg/kg. The human relevance of this finding is unknown.

8.2 Lactation

Risk Summary
There are no data on the presence of teplizumab-mzwv in either human or animal milk, the effects on the breastfed child, or the effects on milk production. Endogenous maternal IgG and monoclonal antibodies are transferred into human milk. The effects of local gastrointestinal exposure and limited systemic exposure in the breastfed infant to teplizumab-mzwv are unknown.

Although the developmental and health benefits of breastfeeding should be considered along with the mother's clinical need for TZIELD and any potential adverse effects on the breastfed child from TZIELD or from the underlying maternal condition, a lactating woman may interrupt breastfeeding and pump and discard breast milk during treatment and for 20 days after TZIELD administration to minimize drug exposure to a breastfed child.

8.4 Pediatric Use

The safety and effectiveness of TZIELD to delay the onset of Stage 3 type 1 diabetes have been established in pediatric patients 8 years of age and older with Stage 2 type 1 diabetes. Use of TZIELD for this indication is supported by evidence from an adequate and well-controlled study (Study TN-10) in adults and pediatric patients 8 years of age and older (including 29 pediatric patients). Adverse reactions observed in pediatric patients 8 years of age and older who received TZIELD were consistent with those reported in adult patients [see Adverse Reactions (6.1)].

The safety and effectiveness of TZIELD have not been established in pediatric patients younger than 8 years of age.

8.5 Geriatric Use

Stage 2 type 1 diabetes is largely a condition that occurs in pediatric and younger adult patients. Clinical studies of TZIELD to delay the onset of Stage 3 T1D did not include patients 65 years of age and older.

11 DESCRIPTION

Teplizumab-mzwv is a CD3-directed monoclonal antibody (humanized IgG1 kappa) that has a molecular weight of approximately 150 kilodalton (kDa) and is expressed from a recombinant Chinese hamster ovary (CHO) cell line.

TZIELD (teplizumab-mzwv) injection is supplied as a sterile, preservative-free, clear and colorless solution in a 2 mg/2 mL (1 mg/mL) single-dose vial for intravenous use. Each mL contains 1 mg of teplizumab-mzwv, dibasic sodium phosphate (0.26 mg), monobasic sodium phosphate (0.98 mg), polysorbate 80 (0.05 mg), sodium chloride (8.78 mg), and water for injection. The pH is 6.1.

12 CLINICAL PHARMACOLOGY

12.1 Mechanism of Action

Teplizumab-mzwv binds to CD3 (a cell surface antigen present on T lymphocytes) and delays the onset of Stage 3 type 1 diabetes in adults and pediatric patients aged 8 years and older with Stage 2 type 1 diabetes. The mechanism may involve partial agonistic signaling and deactivation of pancreatic beta cell autoreactive T lymphocytes. Teplizumab-mzwv leads to an increase in the proportion of regulatory T cells and of exhausted CD8+ T cells in peripheral blood.

12.2 Pharmacodynamics

Clinical studies have shown that teplizumab-mzwv binds to CD3 molecules on the surface of both CD4+ and CD8+ T cells during treatment, with internalization of the teplizumab- mzwv/CD3 complex from the surface of T cells. Pharmacodynamic effects include lymphopenia in the absence of depletion of T cells with a nadir on the 5th day of dosing, during a 14-day course of TZIELD treatment [see Warnings and Precautions (5.3)]. Teplizumab-mzwv exposure-response relationship and time course of pharmacodynamic response for the safety and effectiveness of teplizumab-mzwv have not been fully characterized.

12.3 Pharmacokinetics

Steady state concentrations of teplizumab-mzwv are not expected to be achieved during the 14- day course of TZIELD.

Distribution
The central volume of distribution (Vd) of teplizumab-mzwv was 2.27 L in a 60 kg subject.

Elimination
Teplizumab-mzwv showed saturable binding and elimination. The mean (SD) terminal elimination half-life and clearance of teplizumab-mzwv are 4.5 (0.2) days and 2.7 (0.8) L/day in a 60 kg subject, respectively.

Metabolism
Teplizumab-mzwv is expected to be metabolized into small peptides by catabolic pathways.

Specific Populations
No clinically significant differences in the pharmacokinetics of teplizumab-mzwv were observed based on age (8 to 35 years old), biologic sex, or racial groups (White, Asians).

BSA-based dosing normalizes the exposure to teplizumab-mzwv across body weight.

12.6 Immunogenicity

The observed incidence of anti-drug antibodies is highly dependent on the sensitivity and specificity of the assay. Differences in assay methods preclude meaningful comparisons of the incidence of anti-drug antibodies in the studies described below with the incidence of anti-drug antibodies in other studies, including those of teplizumab-mzwv or of other teplizumab products.

In the placebo-controlled study in patients aged 8 years of age and older with Stage 2 type 1 diabetes (Study TN-10) [see Clinical Studies (14)], approximately 57% of TZIELD-treated patients developed anti-teplizumab-mzwv antibodies, 46% of whom developed neutralizing antibodies. There is insufficient information to characterize the effects of ADA on pharmacokinetics, pharmacodynamics, or effectiveness of TZIELD. There was a higher incidence of rash in TZIELD-treated patients who developed anti-teplizumab-mzwv antibodies compared to those who did not develop anti-teplizumab-mzwv antibodies [see Adverse Reactions (6.1)].

13 NONCLINICAL TOXICOLOGY

13.1 Carcinogenesis, Mutagenesis, Impairment of Fertility

No long-term studies have been performed to assess the carcinogenic potential of teplizumab- mzwv.

No studies have been performed to assess the mutagenic potential of teplizumab-mzwv. As an antibody, teplizumab-mzwv is not expected to interact directly with DNA.

Fertility and reproductive performance were unaffected in female and male mice that received a murine surrogate anti-mouse CD3 antibody administered by the subcutaneous route at doses up to 20 mg/kg.

14 CLINICAL STUDIES

The effectiveness of TZIELD was investigated in a randomized, double-blind, event-driven, placebo-controlled study (Study TN-10; NCT01030861) in 76 patients, 8 to 49 years of age with Stage 2 type 1 diabetes. Stage 2 type 1 diabetes was defined as having both of the following:

1. Two or more of the following pancreatic islet autoantibodies:
  - Glutamic acid decarboxylase 65 (GAD) autoantibodies
  - Insulin autoantibody (IAA)
  - Insulinoma-associated antigen 2 autoantibody (IA-2A)
  - Zinc transporter 8 autoantibody (ZnT8A)
  - Islet cell autoantibody (ICA)
2. Dysglycemia on oral glucose tolerance testing

In this study, patients were randomized to receive TZIELD or placebo once daily by intravenous infusion for 14 days. Patients in the TZIELD group had a total drug exposure that was comparable to the total drug exposure achieved with the recommended total TZIELD dosage [see Dosage and Administration (2.4)]. The primary efficacy endpoint in this study was the time from randomization to development of Stage 3 type 1 diabetes diagnosis.

Baseline Patient Characteristics
In this study, 45% were female; 97% White, 1% Asian, and 1% reported multiracial background; 3% were Hispanic or Latino ethnicity; and 95% were from the United States. The median age was 14 years (72% were <18 years old) (Table 2).

Table 2. Baseline Age Characteristics of Adults and Pediatric Patients 8 Years of Age and Older with Stage 2 Type 1 Diabetes (Study TN-10) [Intent to treat (ITT) population]
 | TZIELD N=44 | Placebo N=32
Age Group
≥ 18 Years | 34% | 19%
< 18 years | 66% | 81%
Pediatric Age Group Quartiles
8 to <11 years | 21% | 25%
11 to <14 years | 27% | 31%
14 to <18 years | 18% | 25%

Baseline Disease Characteristics
Table 3 displays the baseline disease characteristics in Study TN-10.

Table 3. Baseline Disease Characteristics of Adults and Pediatric Patients 8 Years of Age and Older with Stage 2 Type 1 Diabetes (Study TN-10) [Intent to treat (ITT) population]
 | TZIELD N=44 | Placebo N=32
Glucose, mg/dL [The glucose data are area under the time-concentration curve (AUC) values from the oral glucose tolerance test]
median (min, max) | 165 (115, 207) | 154 (103, 200)
HbA1c, %
median (min, max) | 5.2 (4.6, 6.1) | 5.3 (4.3, 5.6)
HLA-DR4
Missing | 5% | 0
Absent | 34% | 34%
Present | 61% | 66%
HLA-DR3
Missing | 5% | 0
Absent | 48% | 53%
Present | 48% | 47%
HLA-DR3/DR4
Both DR3 and DR4 | 25% | 22%
DR3 only | 23% | 25%
DR4 only | 36% | 44%
Missing | 5% | 0
Neither DR3 nor DR4 | 11% | 9%
Autoantibodies Positive (N)
1 | 2% | 0
2 | 27% | 22%
3 | 25% | 16%
4 | 27% | 44%
5 | 18% | 19%
Autoantibody Type Positive
GAD65 | 91% | 88%
IAA | 43% | 34%
IA-2A | 59% | 75%
ICA | 66% | 88%
ZnT8 | 73% | 75%
Abbreviations: HbA1c=hemoglobin A1c, SD=standard deviation, HLA = human leukocyte antigen, GAD65=Glutamic acid decarboxylase 65 (GAD) autoantibodies, IAA=Insulin autoantibody, IA- 2A=Insulinoma-associated antigen 2 autoantibody, ZnT8A=Zinc transporter 8 autoantibody, ICA=Islet cell autoantibody

Efficacy Results
In Study TN-10, Stage 3 type 1 diabetes was diagnosed in 20 (45%) of the TZIELD-treated patients and in 23 (72%) of the placebo-treated patients. A Cox proportional hazards model, stratified by age and oral glucose tolerance test status at randomization, demonstrated that the median time from randomization to Stage 3 type 1 diabetes diagnosis was 50 months in the TZIELD group and 25 months in the placebo group, for a difference of 25 months. With a median follow-up time of 51 months, therapy with TZIELD resulted in a statistically significant delay in the development of Stage 3 type 1 diabetes, hazard ratio 0.41 (95% CI: 0.22 to 0.78; p=0.0066) (Figure 1).

Study TN-10 was not designed to assess whether there were differences in the effectiveness between subgroups based on demographic characteristics or baseline disease characteristics.

Figure 1: Kaplan-Meier Curve of Time to Diagnosis of Stage 3 Type 1 Diabetes in Adult and Pediatric Patients Aged 8 Years and Older with Stage 2 Type 1 Diabetes by Treatment Group (Study TN-10) [ITT population]

16 HOW SUPPLIED / STORAGE AND HANDLING

TZIELD (teplizumab-mzwv) injection is a clear and colorless solution (2 mg/2 mL (1 mg/mL)) supplied in a single-dose vial as follows:

Carton Contents | NDC
1 single dose vial | NDC 73650-316-01
10 single dose vials | NDC 73650-316-10
14 single dose vials | NDC 73650-316-14

Refrigerate TZIELD vials at 2°C to 8°C (36°F to 46°F) in the original carton to protect from light. Store upright. Do not freeze or shake the vials.

If not used immediately, store the diluted solution at room temperature [15°C to 30°C (59°F to 86°F)] and complete infusion within 4 hours of the start of preparation. Discard the diluted solution if not administered within 4 hours of preparation [see Dosage and Administration (2.5)].

17 PATIENT COUNSELING INFORMATION

Advise the patient to read the FDA-approved patient labeling (Medication Guide).

Cytokine Release Syndrome
Inform patients about the signs and symptoms of CRS [see Warnings and Precautions (5.1)].

Serious Infections
Inform patients that TZIELD may lower the ability of the immune system to fight infections. Instruct patients to contact their health care provider if they develop any symptoms of infection [see Warnings and Precautions (5.2)].

Lymphopenia
Inform patients that although most TZIELD-treated patients had mild lymphopenia; a few had severe lymphopenia that required stopping TZIELD [see Warnings and Precautions (5.3)].

Hypersensitivity Reactions
Advise patients on the symptoms of hypersensitivity reactions and instruct them to stop taking TZIELD and seek medical attention promptly if such symptoms occur [see Warnings and Precautions (5.4)].

Vaccinations
Advise patient to receive all age-appropriate vaccinations prior to starting TZIELD and avoid concurrent use of live, inactivated, and mRNA vaccines with TZIELD [see Warnings and Precautions (5.5)].

Pregnancy
Advise patients to inform their health care provider of a known or suspected pregnancy. Advise patients who are exposed to TZIELD during pregnancy to contact Provention Bio, Inc.'s Adverse Event reporting line at 1-800-633-1610 [see Use in Specific Populations (8.1)].

Lactation
Advise a lactating woman that she may interrupt breastfeeding and pump and discard breast milk during treatment and for 20 days after TZIELD administration to minimize drug exposure to a breastfed infant [see Use in Specific Populations (8.2)].

Manufactured by:
Provention Bio, Inc.
Morristown, NJ 07960
A SANOFI COMPANY

U.S. License Number: 2170
TZIELD is a registered trademark of Provention Bio, Inc.
Copyright © 2025, Provention Bio, Inc. All rights reserved.

MEDICATION GUIDE
TZIELD® (TEE-zeeld)
(teplizumab-mzwv)
injection, for intravenous use

What is the most important information I should know about TZIELD?
TZIELD may cause serious side effects, including:

- Cytokine Release Syndrome (CRS). Signs and symptoms of CRS problems may include:
  - fever
  - feeling tired (fatigue)
  - muscle and joint pain
  - nausea
  - headache
  - increased liver enzymes in your blood
  These signs and symptoms may start during the first 5 days of TZIELD treatment. Tell your healthcare provider right away if you develop any signs and symptoms of CRS during treatment with TZIELD.
- Decrease in white blood cells. TZIELD may cause a decrease in a type of white blood cell called lymphocytes. A decrease in white blood cells is a serious, but common side effect that can affect your body's ability to fight infections. A decrease in white blood cell counts can happen after your first dose. Your white blood cell counts will start to go back to normal after your fifth dose of TZIELD. Some people may develop longer and more severe decreases in lymphocytes.

Your healthcare provider will do blood tests to check your liver and your complete blood counts before you start treatment and during treatment with TZIELD. During and after your treatment with TZIELD, your healthcare provider will check for serious side effects, as well as other side effects, and treat you as needed. Your healthcare provider may temporarily or completely stop your treatment with TZIELD, if you develop liver problems, have a serious infection, or if your blood counts stay too low.
See "What are the possible side effects of TZIELD?" for more information about side effects.

What is TZIELD?
TZIELD is a prescription medicine used to delay the onset of Stage 3 type 1 diabetes, which is when your body can't make enough insulin on its own and may require insulin injections. TZIELD is for adults and children 8 years of age and older who have Stage 2 type 1 diabetes. This means that they have tested positive for 2 or more type 1 diabetes-related autoantibodies, have abnormal blood sugar levels and do not have type 2 diabetes.
It is not known if TZIELD is safe and effective in children under 8 years of age.

Before or after receiving TZIELD, tell your healthcare provider about all your medical conditions, including if you:

- have any of the conditions or symptoms listed in the section "What is the most important information I should know about TZIELD?"
- have a serious infection or an infection that does not go away or that keeps coming back (chronic).
- have recently received or are scheduled to receive an immunization (vaccine). TZIELD may affect how well a vaccine works. Tell your healthcare provider that you are receiving treatment with TZIELD before receiving a vaccine.
- are pregnant or plan to become pregnant. TZIELD may harm your unborn baby. Do not receive TZIELD during pregnancy and at least 30 days before a planned pregnancy.
- If you become pregnant while taking TZIELD, you are encouraged to report your pregnancy to the Provention Bio's Adverse Event reporting line at 1-800-633-1610.
- are breastfeeding or plan to breast feed. It is not known if TZIELD passes into your breast milk and if it can harm your baby. Talk to your healthcare provider about the best way to feed your baby if you receive TZIELD. If you are breastfeeding, you may consider pumping and throwing away your breast milk during treatment with TZIELD and for 20 days after receiving TZIELD treatment.

Tell your healthcare provider about all the medicines you take, including prescription and over-the-counter medicines, vitamins, and herbal supplements.

How will I receive TZIELD?

- TZIELD is given by a healthcare provider through a needle placed in a vein (intravenous infusion) in your arm.
- You will receive a TZIELD infusion one-time a day, every day, for 14 days. Each TZIELD infusion will last about 30 minutes.
- For the first 5 days of treatment, your healthcare provider will give you medicines by mouth before starting your TZIELD infusion. These medicines include ibuprofen, naproxen or other pain relievers such as acetaminophen, an antihistamine, and an anti-nausea medicine. These medicines may help reduce symptoms of CRS such as a fever, headache, muscle and joint pain, or nausea.
- If you miss a scheduled infusion, your healthcare provider will continue your treatment on the next scheduled day. You will not receive 2 infusions on the same day.

Tell your healthcare provider if you think something will stop you from completing treatment with TZIELD.

What are the possible side effects of TZIELD?
TZIELD may cause serious side effects including:

- See "What is the most important information I should know about TZIELD?"

The most common side effects of TZIELD include:

- rash
- leukopenia (decrease in white blood cell counts)
- headache

These are not all of the possible side effects of TZIELD. For more information, ask your healthcare provider or pharmacist. Call your doctor for medical advice about side effects. You may report side effects to the FDA at 1-800-FDA-1088. You may also report side effects to Provention Bio at 1-800-633-1610.

General information about the safe and effective use of TZIELD.
Medicines are sometimes prescribed for purposes other than those listed in a Medication Guide. You can ask your pharmacist or healthcare provider for information about TZIELD that is written for health professionals.

What are the ingredients in TZIELD?
Active ingredient: teplizumab-mzwv.
Inactive ingredients: dibasic sodium phosphate, monobasic sodium phosphate, polysorbate 80, sodium chloride, and water for injection.

Manufactured by:
Provention Bio, Inc.
Morristown, NJ 07960
A SANOFI COMPANY
U.S. License Number: 2170
TZIELD is a registered trademark of Provention Bio, Inc.
Copyright © 2025, Provention Bio, Inc. All rights reserved.
For more information, call 1-800-633-1610 or go to www.tzield.com.

This Medication Guide has been approved by the U.S. Food and Drug Administration.

Issued: 04/2025

PACKAGE LABEL

Package Label - 1 count - 2 mg/2 mL Single-use Vial

PRINCIPAL DISPLAY PANEL

NDC 73650-316-01

Rx only

Tzield™

(teplizumab-mzwv)

INJECTION

2 mg/2 mL (1 mg/1 mL)

Contains 1 single dose vial.
Discard unused portion.

For intravenous infusion after dilution.

Store in the original carton
to protect from light.

Dispense the accompanying
Medication Guide to each patient.

proventionbio

PACKAGE LABEL

Package Label - 10 count - 2 mg/2 mL Single-use Vial

PRINCIPAL DISPLAY PANEL

NDC 73650-316-10

Rx only

Tzield™

(teplizumab-mzwv)

INJECTION

2 mg/2 mL (1 mg/1 mL)

Contains 10 single dose vials.
Discard unused portion.

For intravenous infusion after dilution.

Store in the original carton to protect
from light.

Dispense the accompanying
Medication Guide to each patient.

proventionbio

PACKAGE LABEL

Package Label - 14 count - 2 mg/2 mL Single-use Vial

PRINCIPAL DISPLAY PANEL

NDC 73650-316-14

Rx only

Tzield™

(teplizumab-mzwv)

INJECTION

2 mg/2 mL (1 mg/1 mL)

Contains 14 single dose vials.
Discard unused portion.

For intravenous infusion after dilution.

Store in the original carton to protect
from light.

Dispense the accompanying
Medication Guide to each patient.

proventionbio